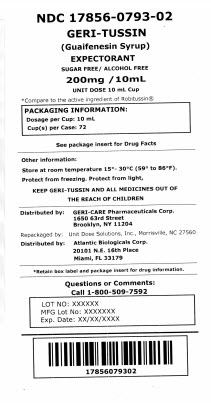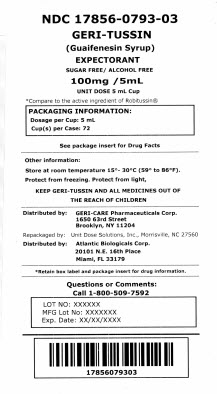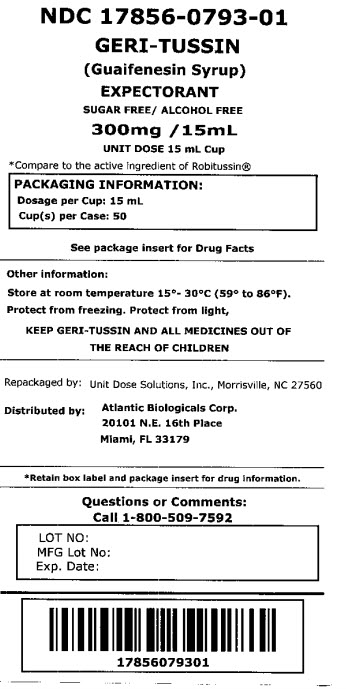 DRUG LABEL: GERI-TUSSIN EXPECTORANT
NDC: 17856-0793 | Form: LIQUID
Manufacturer: Atlantic Biologicals Corps
Category: otc | Type: HUMAN OTC DRUG LABEL
Date: 20180620

ACTIVE INGREDIENTS: GUAIFENESIN 100 mg/5 mL
INACTIVE INGREDIENTS: ANHYDROUS CITRIC ACID; CARAMEL; FD&C RED NO. 40; GLYCERIN; MENTHOL, UNSPECIFIED FORM; SODIUM BENZOATE; SACCHARIN SODIUM; SORBITOL; WATER

Active ingredient (per teaspoonful = 5mL)

Guaifenesin, USP 100 mg

Purpose

Expectorant

Uses

helps loosen phlegm (mucus) and thin bronchial secretions to make coughs more productive

Warnings

Do not use if you are hypersensitive to any of the ingredients

Ask a doctor before use if you have

- cough that occurs with too much phlegm (mucus)
- cough that lasts or is chronic such as occurs with smoking, asthma, chronic bronchitis, or emphysema

Stop use and ask a doctor ifcough lasts more than 7 days, comes back, or is accompanied by fever, rash, or persistent headache. These could be signs of a serious condition.

If pregnant or breast-feeding, ask a health professional before use.

Keep out of reach of children. In case of overdose, get medical help or contact a Poison Control Center right away.

Directions

- do not take more than 6 doses in any 24-hour period
- do not exceed recommended dose

adults and children 12 years and over | 2-4 teaspoonfuls every 4 hours
children under 12 years | ask a doctor

Other information

• store at room temperature 15º - 30ºC (59º - 86ºF)

• protect from freezing

• protect from light

• TAMPER EVIDENT: DO NOT USE THIS PRODUCT IF BREAKAWAY BAND ON CAP IS BROKEN OR MISSING

Inactive ingredients

citric acid, caramel, FD and C Red 40, flavor, glycerin, menthol, sodium saccharin, sodium benzoate, sorbitol, water

HOW SUPPLIED

Product: 17856-0793

NDC: 17856-0793-1 15 mL in a CUP, UNIT-DOSE

NDC: 17856-0793-2 10 mL in a CUP, UNIT-DOSE

NDC: 17856-0793-3 5 mL in a CUP, UNIT-DOSE

GERI-TUSSIN EXPECTORANT (GUAIFENESIN) LIQUID

NDC 17856-0793-1

NDC 17856-0793-2

NDC 17856-0793-03